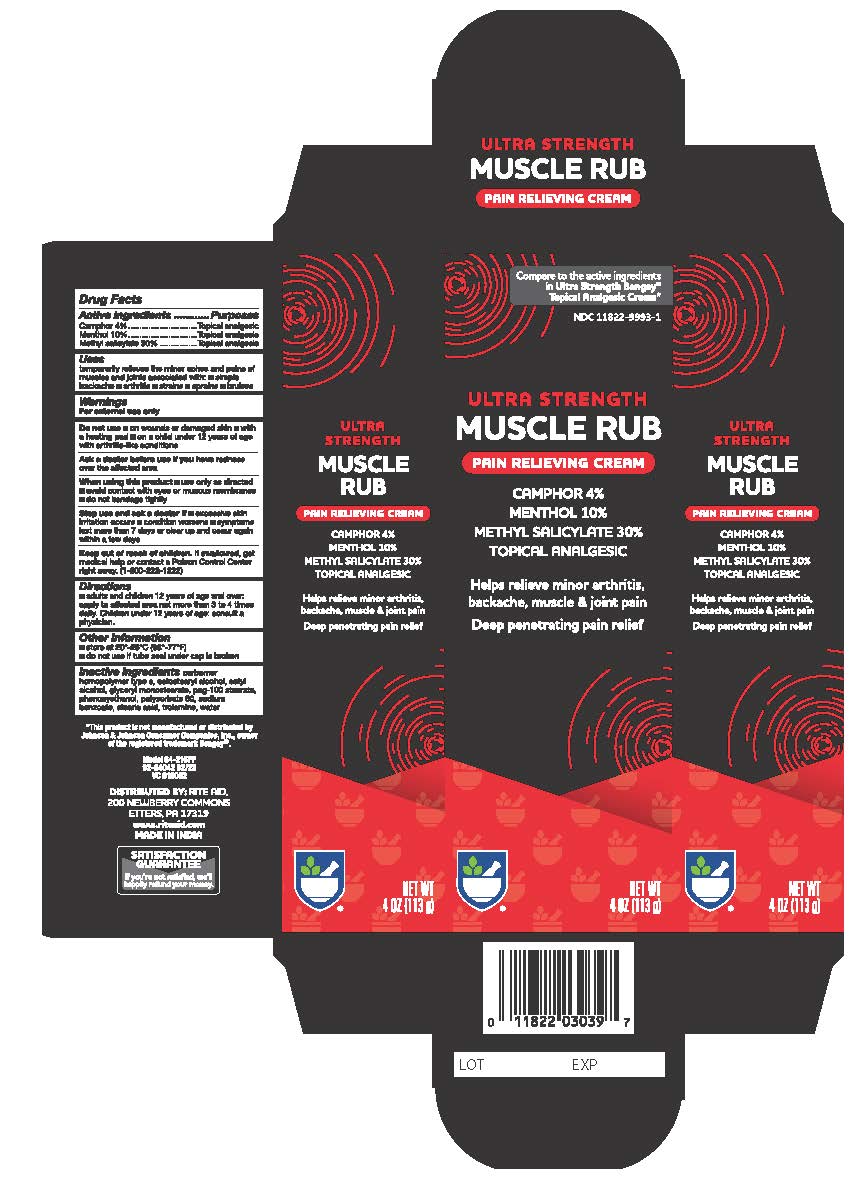 DRUG LABEL: Rite Aid Ultra Strength Muscle Rub
NDC: 11822-9993 | Form: CREAM
Manufacturer: Rite Aid Corporation
Category: otc | Type: HUMAN OTC DRUG LABEL
Date: 20241218

ACTIVE INGREDIENTS: MENTHOL, UNSPECIFIED FORM 100 mg/1 g; CAMPHOR (SYNTHETIC) 40 mg/1 g; METHYL SALICYLATE 300 mg/1 g
INACTIVE INGREDIENTS: PHENOXYETHANOL; STEARIC ACID; CETYL ALCOHOL; POLYSORBATE 60; GLYCERYL MONOSTEARATE; CARBOMER 940; WATER; CETOSTEARYL ALCOHOL; POLYOXYL 100 STEARATE; TROLAMINE; SODIUM BENZOATE

Rite Aid Ultra Strength Muscle Rub

Active Ingredient

Camphor 4%

Menthol 10%

Methyl salicylate 30%

Purpose

Topical Analgesic

Topical Analgesic

Topical Analgesic

Directions

temporarily relieves the minor aches and pains of muscles and joints associated with:

- simple backache
- arthritis
- strains
- bruises
- sprains

Warnings

For external use only.

Do not Use

- on wounds or damaged skin
- with a heating pad
- on a child under 12 years of age with arthritis-like conditions

Ask Doctor

Ask a doctor before use if you have redness over affected area

When Using Section

- use only as directed
- avoid contact with eyes or mucous membranes
- do not bandage tightly

Stop use and ask a doctor if

- condition worsens
- symptoms last more than 7 days or clear up and occur again within a few days

Keep out of reach of children

If swallowed, get medical help or contact a Poison Control Center right away. (1-800-222-1222)

Directions

- adults and children 12 years of age and older: apply to affected area not more than 3 to 4 times daily
- children under 12 years of age: consult a physician

Other Information

- store at 20° to 25°C (68° to 77°F)
- do not use if tube seal under cap is broken

Inactive Ingredients

carbomer homopolymer type C, cetostearyl alcohol, cetyl alcohol, glycerine monostearate, peg-100 stearate, Phenoxyethanol, polysorbate 60, sodium benzoate, stearic acid, trolamine, water

Questions

www.riteaid.com